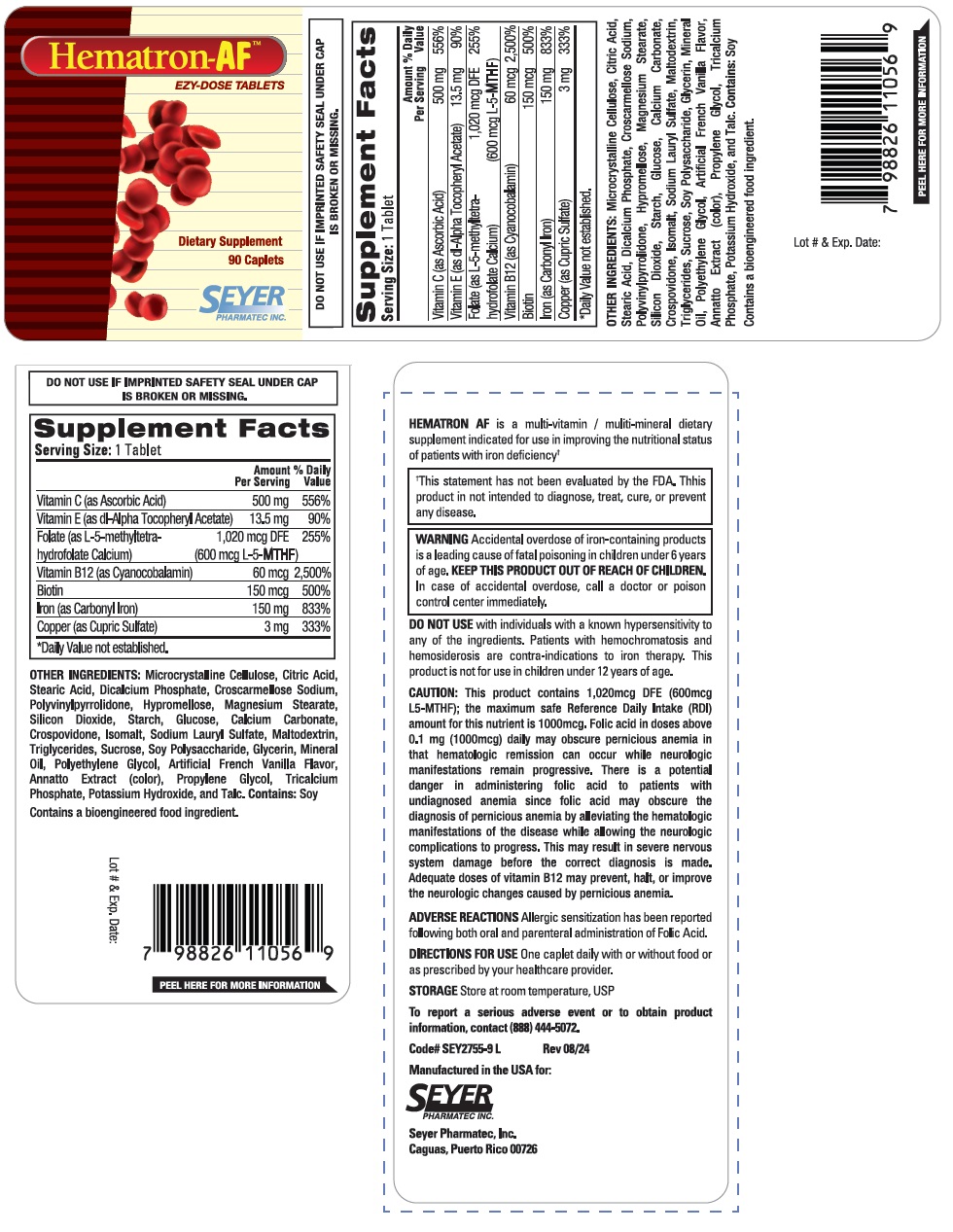 DRUG LABEL: Hematron-AF
NDC: 11026-2761 | Form: TABLET
Manufacturer: Seyer Pharmatec, Inc.
Category: other | Type: DIETARY SUPPLEMENT
Date: 20240813

ACTIVE INGREDIENTS: ASCORBIC ACID 500 mg/1 1; .ALPHA.-TOCOPHEROL ACETATE, DL- 13.5 mg/1 1; LEVOMEFOLATE CALCIUM 600 ug/1 1; CYANOCOBALAMIN 60 ug/1 1; BIOTIN 150 ug/1 1; IRON 150 mg/1 1; CUPRIC SULFATE 3 mg/1 1
INACTIVE INGREDIENTS: MICROCRYSTALLINE CELLULOSE; CITRIC ACID MONOHYDRATE; STEARIC ACID; ANHYDROUS DIBASIC CALCIUM PHOSPHATE; CROSCARMELLOSE SODIUM; POVIDONE, UNSPECIFIED; HYPROMELLOSE, UNSPECIFIED; MAGNESIUM STEARATE; SILICON DIOXIDE; STARCH, RICE; ANHYDROUS DEXTROSE; CALCIUM CARBONATE; CROSPOVIDONE, UNSPECIFIED; ISOMALT; SODIUM LAURYL SULFATE; MALTODEXTRIN; MEDIUM-CHAIN TRIGLYCERIDES; SUCROSE; SOYBEAN COTYLEDON CELL WALL POLYSACCHARIDES; GLYCERIN; MINERAL OIL; POLYETHYLENE GLYCOL, UNSPECIFIED; ANNATTO; PROPYLENE GLYCOL; TRICALCIUM PHOSPHATE; POTASSIUM HYDROXIDE; TALC

Hematron-AF™

STATEMENT OF IDENTITY

Supplement Facts
Serving Size: 1 Tablet
 | Amount | % Daily
 | Per Serving | Value
Vitamin C (as Ascorbic Acid) | 500 mg | 556%
Vitamin E (as dl-Alpha Tocopheryl Acetate) | 13.5 mg | 90%
Folate (as L-5-methyltetrahydrofolate Calcium) | 1,020 mcg DFE | 255%
 | (600 mcg L-5-MTHF)
Vitamin B12 (as Cyanocobalamin) | 60 mcg | 2,500%
Biotin | 150 mcg | 500%
Iron (as Carbonyl Iron) | 150 mg | 833%
Copper (as Cupric Sulfate) | 3 mg | 333%
*Daily Value not established.

OTHER INGREDIENTS:
Microcrystalline Cellulose, Citric Acid, Stearic Acid, Dicalcium Phosphate, Croscarmellose Sodium, Polyvinylpyrrolidone, Hypromellose, Magnesium Stearate, Silicon Dioxide, Starch, Glucose, Calcium Carbonate, Crospovidone, Isomalt, Sodium Lauryl Sulfate, Maltodextrin, Triglycerides, Sucrose, Soy Polysaccharide, Glycerin, Mineral Oil, Polyethylene Glycol, Artificial French Vanilla Flavor, Annatto Extract (color), Propylene Glycol, Tricalcium Phosphate, Potassium Hydroxide, and Talc. Contains: Soy

Contains a bioengineered food ingredient.

HEMATRON AF is a multi-vitamin / multi-mineral dietary supplement indicated for use in improving the nutritional status of patients with iron deficiency†

†This statement has not been evaluated by the FDA. This product is not intended to diagnose, treat, cure, or prevent any disease.

WARNINGS

WARNING Accidental overdose of iron-containing products is a leading cause of fatal poisoning in children under 6 years of age. KEEP THIS PRODUCT OUT OF REACH OF CHILDREN. In case of accidental overdose, call a doctor or poison control center immediately.

DO NOT USE with individuals with a known hypersensitivity to any of the ingredients. Patients with hemochromatosis and hemosiderosis are contra-indications to iron therapy. This product is not for use in children under 12 years of age.

CAUTION:

This product contains 1,020mcg DFE (600mcg L5-MTHF); the maximum safe Reference Daily Intake (RDI) amount for this nutrient is 1000mcg. Folic Acid in doses above 0.1 mg (1000mcg) daily may obscure pernicious anemia in that hematologic remission can occur while neurologic manifestations remain progressive. There is a potential danger in administering folic acid to patients with undiagnosed anemia since folic acid may obscure the diagnosis of pernicious anemia by alleviating the hematologic manifestations of the disease while allowing the neurologic complications to progress. This may result in severe nervous system damage before the correct diagnosis is made. Adequate doses of vitamin B12 may prevent, halt, or improve the neurologic changes caused by pernicious anemia.

ADVERSE REACTIONS

Allergic sensitization has been reported following both oral and parenteral administration of Folic Acid.

DIRECTIONS FOR USE

One caplet daily with or without food or as prescribed by your healthcare provider.

STORAGE

Store at room temperature, USP.

To report a serious adverse event or to obtain product information, contact (888) 444-5072.

Manufactured in the USA for:
Seyer Pharmatec, Inc.
Caguas, Puerto Rico 00726

DO NOT USE IF IMPRINTED SAFETY SEAL UNDER CAP IS BROKEN OR MISSING.

HEALTH CLAIM

Dietary Supplement

EZY-DOSE TABLETS